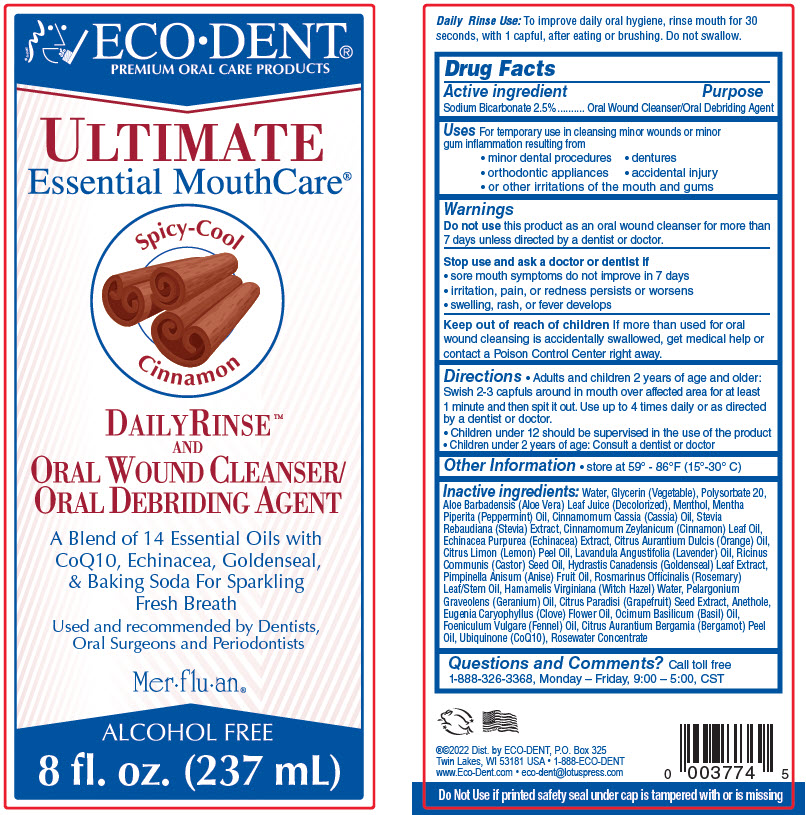 DRUG LABEL: EcoDent Ultimate Essential Mouthcare 
NDC: 76328-221 | Form: LIQUID
Manufacturer: Lotus Brands, Inc.
Category: otc | Type: HUMAN OTC DRUG LABEL
Date: 20241218

ACTIVE INGREDIENTS: SODIUM BICARBONATE 25 mg/1 mL
INACTIVE INGREDIENTS: WATER; GLYCERIN; POLYSORBATE 20; CHINESE CINNAMON OIL; CINNAMON LEAF OIL; WITCH HAZEL; STEVIA REBAUDIUNA LEAF; ALOE VERA LEAF; CITRUS PARADISI SEED; UBIDECARENONE; ECHINACEA PURPUREA WHOLE; GOLDENSEAL; CLOVE OIL; ANETHOLE; PELARGONIUM GRAVEOLENS FLOWER OIL; PEPPERMINT OIL; MENTHOL, UNSPECIFIED FORM; ORANGE OIL, COLD PRESSED; CITRUS X LIMON SEED OIL; STAR ANISE OIL; BERGAMOT OIL; BASIL OIL; FENNEL OIL; ROSEMARY OIL; SULFATED CASTOR OIL; LAVENDER OIL; ROSA X DAMASCENA FLOWER OIL

EcoDent® Ultimate Essential Mouthcare®
Spicy-Cool Cinnamon

Drug Facts

Active ingredient

Sodium Bicarbonate 2.5%

Purpose

Oral Wound Cleanser/Oral Debriding Agent

Uses

For temporary use in cleansing minor wounds or minor gum inflammation resulting from

- minor dental procedures
- dentures
- orthodontic appliances
- accidental injury
- or other irritations of the mouth and gums

Warnings

Do not use this product as an oral wound cleanser for more than 7 days unless directed by a dentist or doctor

Stop use and ask a doctor or dentist if

- sore mouth symptoms do not improve in 7 days
- irritation, pain, or redness persists or worsens
- swelling, rash, or fever develops

Keep out of reach of children

If more than used for oral wound cleansing is accidentally swallowed, get medical help or contact a Poison Control Center right away

Directions

- Adults and children 2 years of age and older: Swish 2-3 capfuls around in mouth over affected area for at least 1 minute and then spit it out. Use up to 4 times daily or as directed by a dentist or doctor
- Children under 12 should be supervised in the use of the product
- Children under 2 years of age: Consult a dentist or doctor

Other Information

- store at 59° - 86°F (15°-30° C)

Inactive ingredients

Aqua (Purified Water), Glycerin (Vegetable), Polysorbate 20, Aloe Barbadensis (Aloe Vera) Leaf Juice (Decolorized), Menthol, Mentha Piperita (Peppermint) Oil, Cinnamomum Cassia (Cassia) Oil, Stevia Rebaudiana (Stevia) Extract, Cinnamomum Zeylanicum (Cinnamon) Leaf Oil, Echinacea Purpurea (Echinacea) Extract, Citrus Aurantium Dulcis (Orange) Oil, Citrus Limon (Lemon) Peel Oil, Lavandula Angustifolia (Lavender) Oil, Ricinus Communis (Castor) Seed Oil, Hydrastis Canadensis (Goldenseal) Leaf Extract, Pimpinella Anisum (Anise) Fruit Oil, Rosmarinus Officinalis (Rosemary) Leaf/Stem Oil, Hamamelis Virginiana (Witch Hazel) Water, Pelargonium Graveolens (Geranium) Oil, Citrus Paradisi (Grapefruit) Seed Extract, Anethole, Eugenia Caryophyllus (Clove) Flower Oil, Ocimum Basilicum (Basil) Oil, Foeniculum Vulgare (Fennel) Oil, Citrus Aurantium Bergamia (Bergamot) Peel Oil, Ubiquinone (CoQ10), Rosewater Concentrate

Questions and Comments?

Call toll free 1-888-326-3368, Monday – Friday, 9:00 – 5:00, CST

Dist. by ECO-DENT
P.O. Box 325
Twin Lakes, WI 53181 USA

PRINCIPAL DISPLAY PANEL - 237 mL Bottle Label

ECO•DENT®
PREMIUM ORAL CARE PRODUCTS

ULTIMATE
Essential MouthCare®

Spicy-Cool
Cinnamon

DAILYRINSE™
AND
ORAL WOUND CLEANSER/
ORAL DEBRIDING AGENT

A Blend of 14 Essential Oils with
CoQ10, Echinacea, Goldenseal,
& Baking Soda For Sparkling
Fresh Breath

Used and recommended by Dentists,
Oral Surgeons and Periodontists

Mer•flu•an®

ALCOHOL FREE
8 fl. oz. (237 mL)